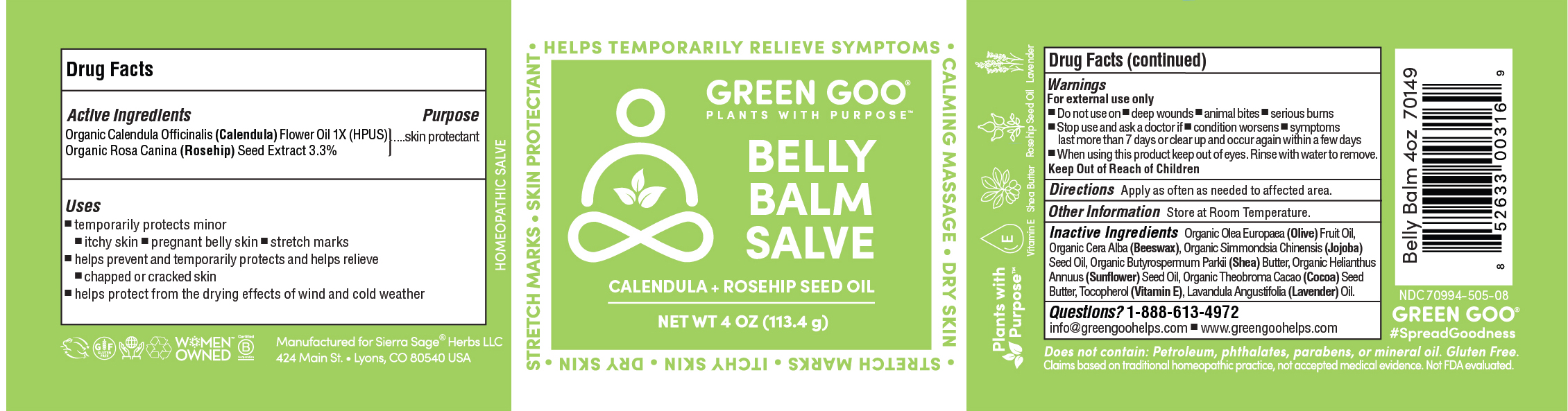 DRUG LABEL: Belly Balm
NDC: 70994-506 | Form: SALVE
Manufacturer: Spry Life LLC
Category: homeopathic | Type: HUMAN OTC DRUG LABEL
Date: 20251215

ACTIVE INGREDIENTS: ROSA MOSCHATA OIL 3.3 g/100 g; CALENDULA OFFICINALIS FLOWER 1 [hp_X]/100 g
INACTIVE INGREDIENTS: TOCOPHEROL; LAVENDER OIL; COCOA BUTTER; YELLOW WAX; JOJOBA OIL; SHEA BUTTER; OLIVE OIL; SUNFLOWER OIL

Belly Balm

Purpose Section

Skin Protectant

Active Ingredients

Organic Calendula Officinalis (Calendula) Flower Oil 1X (HPUS)

Organic Rosa Canina (Rosehip) Seed Extract 3.3%

Indications & Usage

■ temporarily protects minor ■ itchy skin ■ pregnant belly skin ■ stretch marks

■ helps prevent and temporarily protects and helps relieve ■ chapped or cracked skin

■ helps protect from the drying effects of wind and cold weather

Keep out of reach of children section

Keep out of reach of children.

Warnings Section

Warnings

For external use only.

■ Do not use on ■ on deep wounds ■ animal bites ■ serious burns

■ Stop use and ask a doctor if ■ condition worsens ■ symptoms last more than 7 days or clear up and occur again within a few days

■ When using this product keep out of eyes. Rinse with water to remove.

Storage

Store at room temperature.

Dosage & Administration Section

Apply as often as needed to pregnant belly.

Inactive Ingredients

Organic Olea Europaea (Olive) Fruit Oil, Organic Cera Alba (Beeswax), Organic Simmondsia Chinensis (Jojoba) Seed Oil, Organic Butyrospermum Parkii (Shea) Butter, Organic Helianthus Annuus (Sunflower) Seed Oil, Organic Theobroma Cacao (Cocoa) Seed Butter, Tocopherol (Vitamin E), Lavandula Angustifolia (Lavender) Oil.